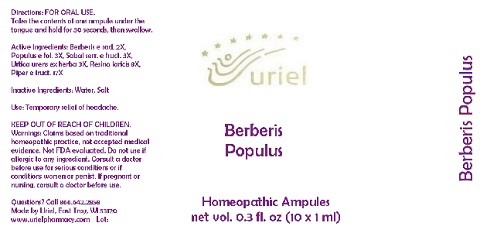 DRUG LABEL: Berberis Populus
NDC: 48951-2047 | Form: LIQUID
Manufacturer: Uriel Pharmacy Inc.
Category: homeopathic | Type: HUMAN OTC DRUG LABEL
Date: 20180521

ACTIVE INGREDIENTS: BERBERIS VULGARIS ROOT BARK 2 [hp_X]/1 mL; POPULUS TREMULA WHOLE 3 [hp_X]/1 mL; SAW PALMETTO 3 [hp_X]/1 mL; URTICA URENS 3 [hp_X]/1 mL; LARIX DECIDUA RESIN 8 [hp_X]/1 mL; BLACK PEPPER 17 [hp_X]/1 mL
INACTIVE INGREDIENTS: WATER; SODIUM CHLORIDE

Berberis Populus

INDICATIONS AND USAGE

Directions: FOR ORAL USE.

DOSAGE AND ADMINISTRATION

Take the contents of one ampule under the tongue and hold for 30 seconds, then swallow.

ACTIVE INGREDIENT

Active Ingredients: Berberis e rad. 2X, Populus e fol. 3X, Sabal serr. e fruct. 3X, Urtica urens ex herba 3X, Resina laricis 8X, Piper e fruct. 17X

Inactive Ingredients: Water, Salt

PURPOSE

Use: Temporary relief of headache.

KEEP OUT OF REACH OF CHILDREN.

WARNINGS

Warnings: Claims based on traditional homeopathic practice, not accepted medical evidence. Not FDA evaluated. Do not use if allergic to any ingredient. Consult a doctor before use for serious conditions or if conditions worsen or persist. If pregnant or nursing, consult a doctor before use.

QUESTIONS

Questions? Call 866.642.2858 Made by Uriel, East Troy, WI 53120 www.urielpharmacy.com